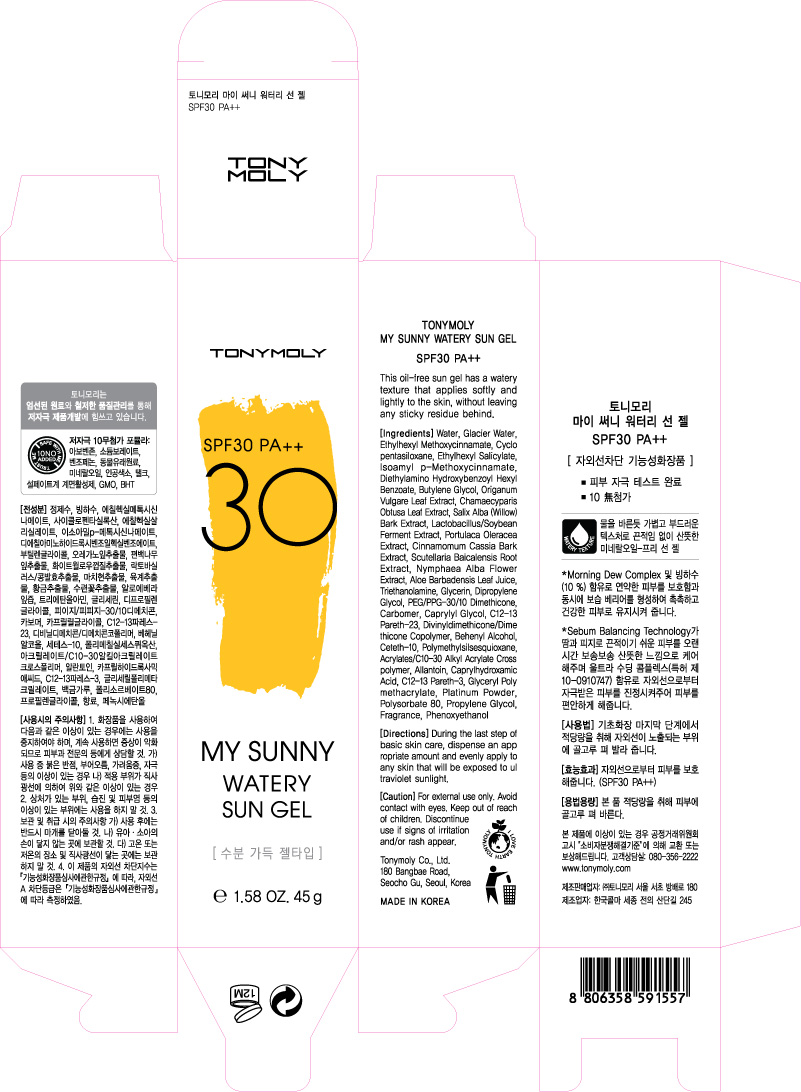 DRUG LABEL: TONYMOLY My Sunny Watery Sun Gel
NDC: 59078-122 | Form: GEL
Manufacturer: Tonymoly Co., Ltd.
Category: otc | Type: HUMAN OTC DRUG LABEL
Date: 20160204

ACTIVE INGREDIENTS: GLYCERIN 0.252 g/45 g
INACTIVE INGREDIENTS: TROLAMINE; OREGANO; CHINESE CINNAMON; NYMPHAEA ALBA FLOWER; ALOE VERA LEAF; SCUTELLARIA BAICALENSIS ROOT; DIPROPYLENE GLYCOL; CAPRYLYL GLYCOL; WATER; POLYSORBATE 80; ALLANTOIN; C12-13 PARETH-23; C12-13 PARETH-3; CAPRYLHYDROXAMIC ACID; PHENOXYETHANOL; CETETH-10; PEG/PPG-30/10 DIMETHICONE; DIETHYLAMINO HYDROXYBENZOYL HEXYL BENZOATE; BUTYLENE GLYCOL; CYCLOMETHICONE 5; AMILOXATE; CHAMAECYPARIS OBTUSA LEAF; OCTISALATE; DOCOSANOL; WILLOW BARK; PORTULACA OLERACEA WHOLE; PROPYLENE GLYCOL; PLATINUM

Active Ingredients

Ethylhexyl Methoxycinnamate 6%

Purpose

Sunscreen

Use

This oil-free sun gel has a watery texture that applies softly and lightly to the skin, without leaving any sticky residue behind.

Caution

For external use only. Avoid contact with eyes. Keep out of reach of children. Discontinue use if signs of irritation and/or rash appear.

Keep out of reach of children

Directions

During the last step of basic skin care, dispense an appropriate amount and evenly apply to any skin that will be exposed to ultraviolet sunlight.

Inactive Ingredients

WATER, CYCLOPENTASILOXANE, ETHYLHEXYL SALICYLATE, ISOAMYL P-METHOXYCINNAMATE, BUTYLENE GLYCOL, DIETHYLAMINO HYDROXYBENZOYL HEXYL BENZOATE, TRIETHANOLAMINE, GLYCERIN, DIPROPYLENE GLYCOL, PEG/PPG-30/10 DIMETHICONE, CARBOMER, CAPRYLYL GLYCOL, C12-13 PARETH-23, DIVINYLDIMETHICONE/DIMETHICONE COPOLYMER, BEHENYL ALCOHOL, CETETH-10, FRAGRANCE, PHENOXYETHANOL, POLYMETHYLSILSESQUIOXANE, ACRYLATES/C10-30 ALKYL ACRYLATE CROSSPOLYMER, ALLANTOIN, CAPRYLHYDROXAMIC ACID, C12-13 PARETH-3, CHAMAECYPARIS OBTUSA LEAF EXTRACT, ORIGANUM VULGARE LEAF EXTRACT, SALIX ALBA (WILLOW) BARK EXTRACT, CINNAMOMUM CASSIA BARK EXTRACT, LACTOBACILLUS/SOYBEAN FERMENT EXTRACT, PORTULACA OLERACEA EXTRACT, SCUTELLARIA BAICALENSIS ROOT EXTRACT, NYMPHAEA ALBA FLOWER EXTRACT, ALOE BARBADENSIS LEAF JUICE, GLYCERYL POLYMETHACRYLATE, PROPYLENE GLYCOL, PLATINUM POWDER, POLYSORBATE 80